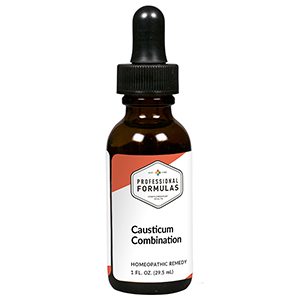 DRUG LABEL: Causticum Combination
NDC: 63083-9253 | Form: LIQUID
Manufacturer: Professional Complementary Health Formulas
Category: homeopathic | Type: HUMAN OTC DRUG LABEL
Date: 20190815

ACTIVE INGREDIENTS: CAUSTICUM 3 [hp_X]/29.5 mL; ARNICA MONTANA WHOLE 4 [hp_X]/29.5 mL; PULSATILLA MONTANA WHOLE 6 [hp_X]/29.5 mL; CALCIUM SULFIDE 8 [hp_X]/29.5 mL; SODIUM DIETHYL OXALACETATE 8 [hp_X]/29.5 mL; OXOGLURIC ACID 10 [hp_X]/29.5 mL; ARSENIC TRIOXIDE 10 [hp_X]/29.5 mL; FUMARIC ACID 10 [hp_X]/29.5 mL; BOS TAURUS PLACENTA 10 [hp_X]/29.5 mL; HISTAMINE DIHYDROCHLORIDE 12 [hp_X]/29.5 mL; SULFUR 12 [hp_X]/29.5 mL
INACTIVE INGREDIENTS: ALCOHOL; WATER

R253

ACTIVE INGREDIENTS

Causticum 3X
Arnica montana 4X
Pulsatilla 6X
Hepar sulphuris calcareum 8X
Natrum oxalaceticum 8X
a-Ketoglutaricum acidum 10X
Arsenicum album 10X
Fumaricum acidum 10X
Placenta 10X
Histaminum hydrochloricum 12X
Sulphur 12X

QUESTIONS

Professional Formulas

PO Box 2034 Lake Oswego, OR 97035

INDICATIONS

For the temporary relief of skin conditions such as minor pain, blistering, or redness due to sunburn, small scalds, or other minor burns.*

PURPOSE

*Claims based on traditional homeopathic practice, not accepted medical evidence. Not FDA evaluated.

WARNINGS

Consult a doctor if condition worsens or if symptoms persist. Keep out of the reach of children. In case of overdose, get medical help or contact a poison control center right away. If pregnant or breastfeeding, ask a healthcare professional before use.

Keep out of the reach of children.

PREGNANCY OR BREAST FEEDING

If pregnant or breastfeeding, ask a healthcare professional before use.

DIRECTIONS

Place drops under tongue 30 minutes before/after meals. Adults and children 12 years and over: Take 10 drops up to 3 times per day. Consult a physician for use in children under 12 years of age.

OTHER INFORMATION

Tamper resistant. If seal is broken, do not use. After opening, close container tightly and store at room temperature away from heat.

INACTIVE INGREDIENTS

40% ethanol, purified water.

LABEL

Est 1985

Professional Formulas

Complementary Health

Causticum Combination

Homeopathic Remedy

1 FL. OZ. (29.5 mL)